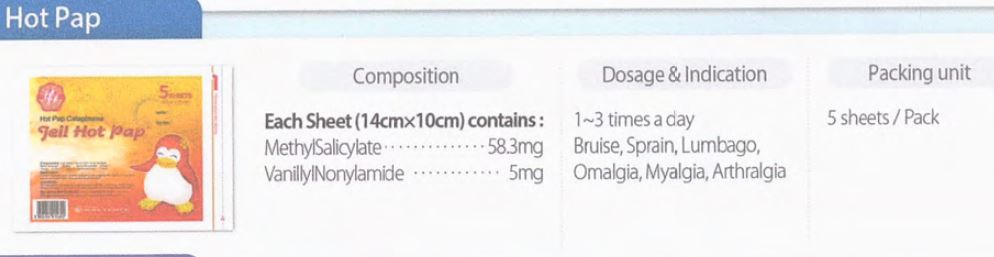 DRUG LABEL: Hot Pap Cataplasma
NDC: 72988-0007 | Form: PATCH
Manufacturer: Lydia Co., Ltd.
Category: otc | Type: HUMAN OTC DRUG LABEL
Date: 20230705

ACTIVE INGREDIENTS: METHYL SALICYLATE 58.3 mg/13.4 g; NONIVAMIDE 5 mg/13.4 g
INACTIVE INGREDIENTS: THYMOL; KAOLIN; GLYCERIN

Drug Facts

ACTIVE INGREDIENT

Methyl salicylate

Vanillyl nonylamide

INACTIVE INGREDIENT

Kaolin

Glycerin

Liquid paraffin

Gelatin

Titanium oxide

Carboxymethylcellulose sodium

Zinc oxide

Methoxyethylene maleicanhydride copolymer

Polybutene

Citric acid hydrate

Sodium polyacrylate

Thymol

Butyl paraben

Butylated hydroxy toluene

Polysorbate 60

Isopropyl myristate

Natural rubber latex

Purified water

Nonwoven fabric

Polyester film

PURPOSE

Topical Analgesic

Temporarily relieves minor pain associated with - muscular pain - joint pain - backache - bruise - sprain

keep out of reach of the children

INDICATIONS AND USAGE

Adults and children 12 years of age and over: apply to affected area not more than 3 to 4 times daily.

Children under 12 years of age: do not use, consult a doctor
For easy application: partially peel back protective film and apply exposed patch to the site of pain.
Carefully remove remaining film while pressing patch to skin for secure adhesion.

WARNINGS

use only as directed
do not bandage tightly or use with a healing pad
avoid contact with the eyes and mucous membranes
do not apply to wounds or damaged skin

DOSAGE AND ADMINISTRATION

for external use only